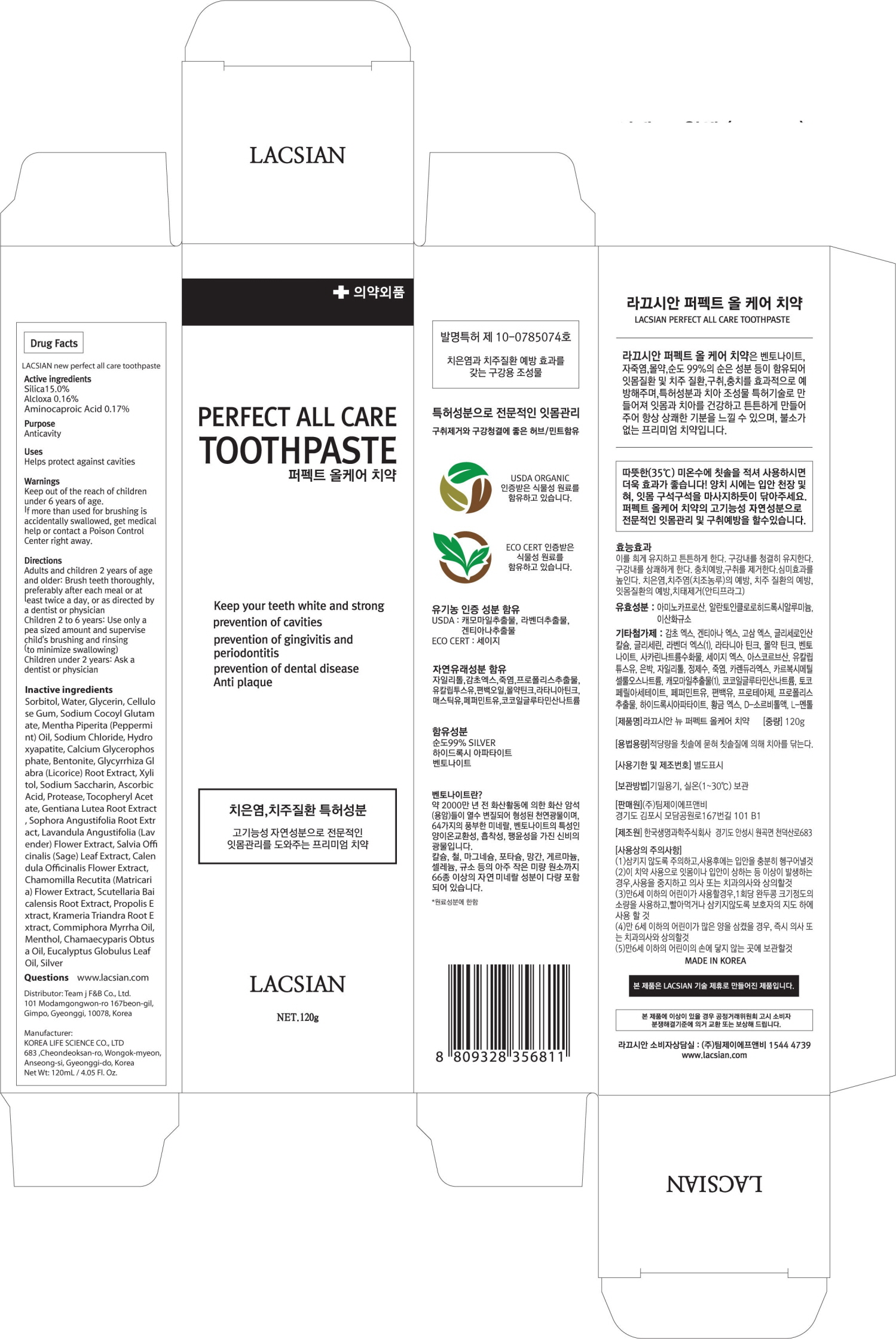 DRUG LABEL: LACSIAN new perfect all care tooth
NDC: 72048-030 | Form: PASTE, DENTIFRICE
Manufacturer: Team J F&B Co., Ltd.
Category: otc | Type: HUMAN OTC DRUG LABEL
Date: 20191127

ACTIVE INGREDIENTS: SILICON DIOXIDE 18.0 g/120 g; ALCLOXA 0.15 g/120 g; Aminocaproic Acid 0.20 g/120 g
INACTIVE INGREDIENTS: Water; Glycerin

ACTIVE INGREDIENT

Active ingredients: Silica 15.0%, Alcloxa 0.13%, Aminocaproic Acid 0.17%

INACTIVE INGREDIENT

Inactive ingredients:

Sorbitol, Water, Glycerin, Cellulose Gum, Sodium Cocoyl Glutamate, Mentha Piperita (Peppermint) Oil, Sodium Chloride, Hydroxyapatite, Calcium Glycerophosphate, Bentonite, Glycyrrhiza Glabra (Licorice) Root Extract, Xylitol, Sodium Saccharin, Ascorbic Acid, Protease, Tocopheryl Acetate, Gentiana Lutea Root Extract, Sophora Angustifolia Root Extract, Lavandula Angustifolia (Lavender) Flower Extract, Salvia Officinalis (Sage) Leaf Extract, Calendula Officinalis Flower Extract, Chamomilla Recutita (Matricaria) Flower Extract, Scutellaria Baicalensis Root Extract, Propolis Extract, Krameria Triandra Root Extract, Commiphora Myrrha Oil, Menthol, Chamaecyparis Obtusa Oil, Eucalyptus Globulus Leaf Oil, Silver

PURPOSE

Purpose: Anticavity

WARNINGS

Keep out of the reach of children under 6 years of age.
If more than used for brushing is accidentally swallowed, get medical help or contact a Poison Control Center right away.

KEEP OUT OF REACH OF CHILDREN

Keep out of the reach of children under 6 years of age.

Uses

Uses: Helps protect against cavities

Directions

Adults and children 2 years of age and older: Brush teeth thoroughly, preferably after each meal or at least twice a day, or as directed by a dentist or physician

Children 2 to 6 years: Use only a pea sized amount and supervise child's brushing and rinsing (to minimize swallowing)

Children under 2 years: Ask a dentist or physician